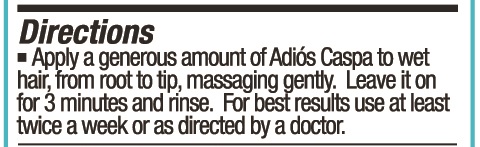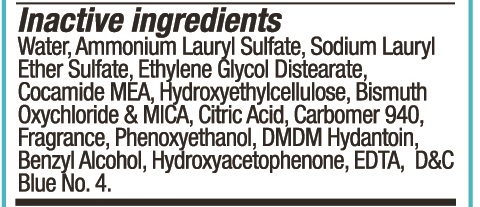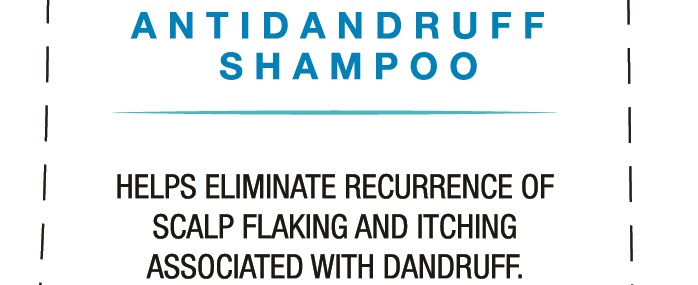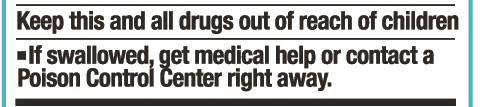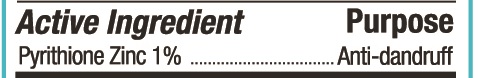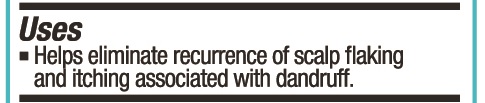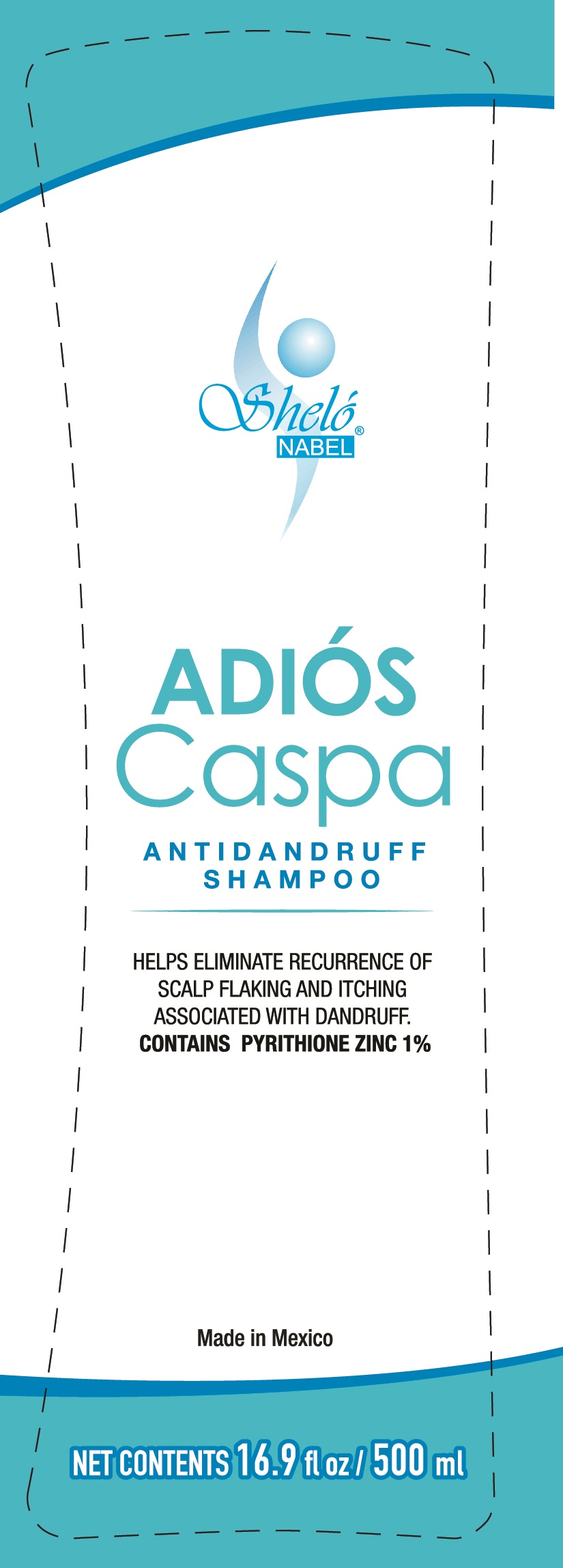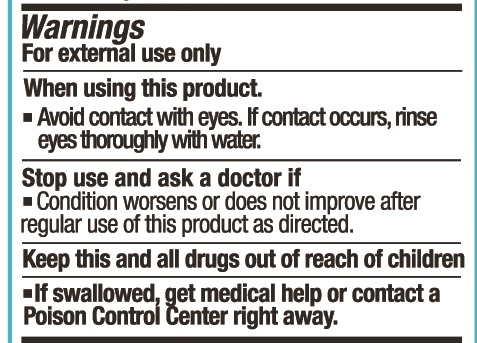 DRUG LABEL: Shelo NABEL Anti Caspa
NDC: 71424-1050 | Form: SHAMPOO
Manufacturer: Corporativo Serysi S de R L de C V
Category: otc | Type: HUMAN OTC DRUG LABEL
Date: 20191015

ACTIVE INGREDIENTS: PYRITHIONE ZINC 10 mg/1 g
INACTIVE INGREDIENTS: AMMONIUM LAURYL SULFATE

Sheló NABEL Adios Caspa